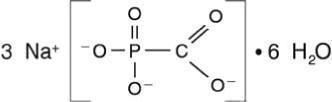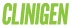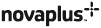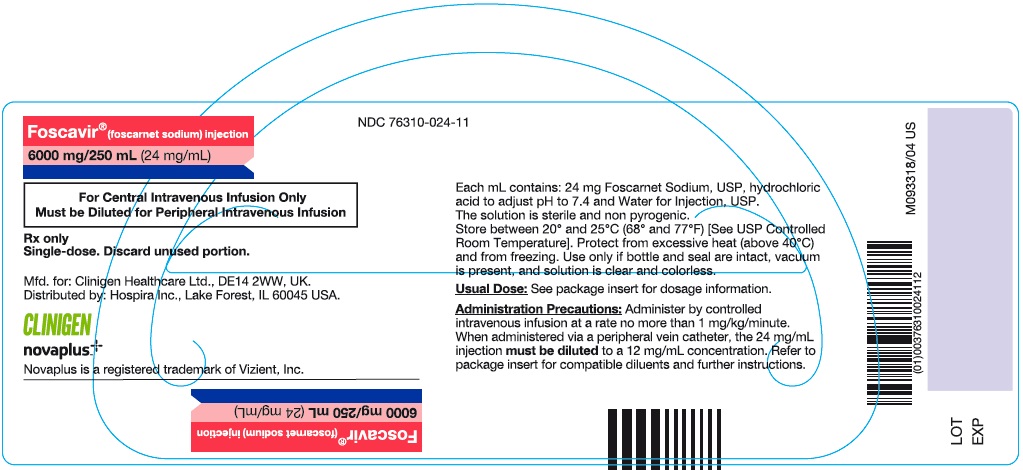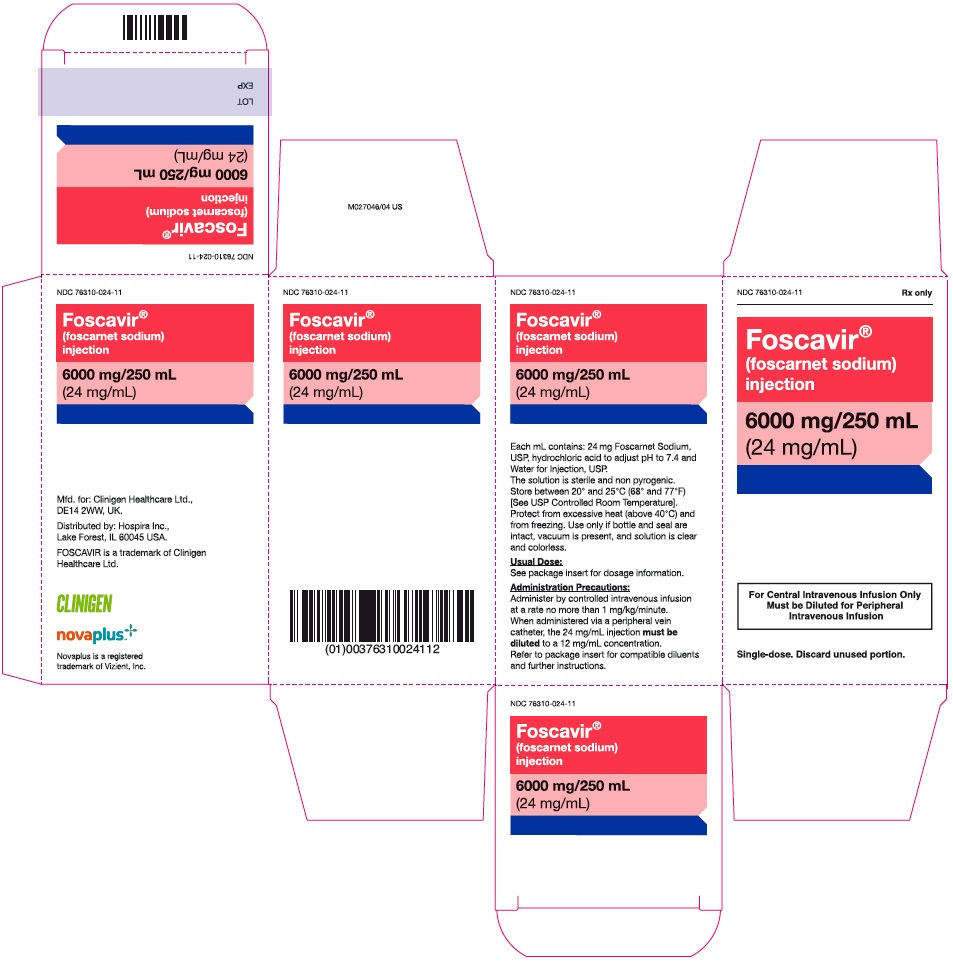 DRUG LABEL: Foscavir
NDC: 76310-024 | Form: INJECTION, SOLUTION
Manufacturer: Clinigen Limited
Category: prescription | Type: HUMAN PRESCRIPTION DRUG LABEL
Date: 20251211

ACTIVE INGREDIENTS: foscarnet sodium 24 mg/1 mL
INACTIVE INGREDIENTS: hydrochloric acid; water

FOSCAVIR ®
(foscarnet sodium) INJECTION

WARNING

RENAL IMPAIRMENT IS THE MAJOR TOXICITY OF FOSCAVIR. FREQUENT MONITORING OF SERUM CREATININE, WITH DOSE ADJUSTMENT FOR CHANGES IN RENAL FUNCTION, AND ADEQUATE HYDRATION WITH ADMINISTRATION OF FOSCAVIR IS IMPERATIVE. (See ADMINISTRATION section; Hydration.)

SEIZURES, RELATED TO ALTERATIONS IN PLASMA MINERALS AND ELECTROLYTES, HAVE BEEN ASSOCIATED WITH FOSCAVIR TREATMENT. THEREFORE, PATIENTS MUST BE CAREFULLY MONITORED FOR SUCH CHANGES AND THEIR POTENTIAL SEQUELAE. MINERAL AND ELECTROLYTE SUPPLEMENTATION MAY BE REQUIRED.

FOSCAVIR IS INDICATED FOR USE ONLY IN IMMUNOCOMPROMISED PATIENTS WITH CMV RETINITIS AND MUCOCUTANEOUS ACYCLOVIR-RESISTANT HSV INFECTIONS. (See INDICATIONS section).

DESCRIPTION

FOSCAVIR is the brand name for foscarnet sodium. The chemical name of foscarnet sodium is phosphonoformic acid, trisodium salt. Foscarnet sodium is a white, crystalline powder containing 6 equivalents of water of hydration with an empirical formula of Na3CO5P•6 H2O and a molecular weight of 300.1. The structural formula is:

FOSCAVIR has the potential to chelate divalent metal ions, such as calcium and magnesium, to form stable coordination compounds. FOSCAVIR INJECTION is a sterile, isotonic aqueous solution for intravenous administration only. The solution is clear and colorless. Each milliliter of FOSCAVIR contains 24 mg of foscarnet sodium hexahydrate in Water for Injection, USP. Hydrochloric acid may have been added to adjust the pH of the solution to 7.4. FOSCAVIR INJECTION contains no preservatives.

VIROLOGY

Mechanism of Action

Foscarnet exerts its antiviral activity by a selective inhibition at the pyrophosphate binding site on virus-specific DNA polymerases at concentrations that do not affect cellular DNA polymerases. Foscarnet does not require activation (phosphorylation) by thymidine kinase or other kinases.

Antiviral Activity in Cell Culture

The quantitative relationship between the cell culture susceptibility of human cytomegalovirus (CMV) or herpes simplex virus 1 and 2 (HSV-1 and HSV-2) to foscarnet and clinical response to therapy has not been established and virus sensitivity testing has not been standardized. Sensitivity test results, expressed as the concentration of drug required to inhibit by 50% the growth of virus in cell culture (EC50), vary greatly depending on the assay method used, cell type employed and the laboratory performing the test. A number of sensitive viruses and their EC50 values are listed below (Table 1). The combination antiviral activity of foscarnet and ganciclovir or acyclovir are not antagonistic in cell culture.

TABLE 1 Foscarnet Inhibition of Virus Replication in Cell Culture
Virus | EC50 value (μM)
CMV Ganciclovir resistant CMV HSV-1, HSV-2 HSV-TK negative mutant HSV-DNA polymerase mutants | 50-800* 190 10-130 67 5-443
*Mean = 269 μM

Antiviral Activity in vivo

Statistically significant decreases in positive CMV cultures from blood and urine have been demonstrated in two studies (FOS-03 and ACTG-015/915) of subjects treated with FOSCAVIR. Although median time to progression of CMV retinitis was increased in subjects treated with FOSCAVIR, reductions in positive blood or urine cultures have not been shown to correlate with clinical efficacy in individual subjects (Table 2).

TABLE 2 Blood and Urine Culture Results from CMV Retinitis Patients*
Blood |  | +CMV | -CMV
Baseline |  | 27 | 34
End of Induction† |  | 1 | 60
Urine |  | +CMV | -CMV
Baseline |  | 52 | 6
End of Induction† |  | 21 | 37
*A total of 77 subjects were treated with FOSCAVIR in two clinical trials (FOS-03 and ACTG-015/915).
Not all subjects had blood or urine cultures done and some subjects had results from both cultures.
†(60 mg/kg FOSCAVIR TID for 2–3 weeks).

Resistance

Cell culture: CMV and HSV isolates with reduced susceptibility to foscarnet have been selected in cell culture by passage of wild type virus in the presence of increasing concentrations of the drug. All foscarnet resistant isolates are known to be generated through amino acid substitutions in the viral DNA polymerase pUL54 (CMV) or pUL30 (HSV) (Table 3).

TABLE 3 Summary of Foscarnet Resistance-associated DNA Polymerase Amino Acid Substitutions in Cell Culture
CMV pUL54 | T419M, T552N, S585A, F595I, Q807A, M844T/V, V946L
HSV-1 pUL30 | Y577H, E597D, A605V, L702H, V714M, L774F, L788M, D780N, L782I, P797T, L802F, V813M, V817M, Y818C, T821M, R842S, S889A, F891C, V892M, D907V, A910V, SRA914-916LCV, V958L, R959H
HSV-2 pUL30 | _

In vivo: Limited clinical data are available on the development of clinical resistance to foscarnet and many pathways to resistance likely exist. Substitutions documented in the literature in treated patients as associated with foscarnet resistance, are listed in Table 4.

TABLE 4 Summary of Foscarnet Resistance-associated Amino Acid Substitutions Observed in Treated Patients
CMV pUL54 | N495K, Q578H/L, D588E/N, T700A, V715M, E756D/K/Q, L773V, L776M, V781I, V787L, L802M, A809V, V812L, T813S, T821I, A834P, T838A, G841A/S, del 981-982
HSV-1 pUL30 | S599L, D672N, R700G, V715G, A719T/V, S724N, E798K, G841C/S, A910T, Y941H
HSV-2 pUL30 | A724T, S725G, S729N, Q732R, L783M, D785N, T844I, L850I, D912V
Note: Many additional pathways to foscarnet resistance likely exist

The possibility of viral resistance should be considered in patients who show poor clinical response or experience persistent viral excretion during therapy.

Cross-Resistance: The amino acid substitutions that resulted in reduced susceptibility to foscarnet and either ganciclovir, acyclovir and/or cidofovir are summarized in Tables 5 and 6.

TABLE 5 Summary of CMV DNA polymerase Amino Acid Substitutions Conferring Foscarnet Resistance with Cross-Resistance to Ganciclovir and/or Cidofovir
Cross-resistant to ganciclovir | CMV pUL54 | Q578H, D588N, E756K, L773V, L776M, V781I, V787L, L802M, A809V, V812L, T813S, T821I, A834P, G841A/S, del 981-982
Cross-resistant to cidofovir | CMV pUL54 | Q578H, D588N, E756K, L773V, V812L, T813S, A834P, G841A, del 981-982

TABLE 6 Summary of HSV DNA polymerase Amino Acid Substitutions Conferring Foscarnet Resistance with Cross-Resistance to Acyclovir and/or Cidofovir
Cross-resistant to; acyclovir | HSV-1 pUL30 | E597D, S599L, A605V, D672N, R700G, L702H, V714M, V715G, A719T/V, S724N, L774F, L778M, D780N, L782I, P797T, E798K, L802F, V813M, V817M, Y818C, T821M, G841C/S, R842S, S889A, F891C/Y, V892M, D907V, A910V/T, SRA914-916LCV, Y941H, V958L, V959H
Cross-resistant to; acyclovir | HSV-2 pUL30 | A724T, S725G, S729N, Q732R, L783M, D785N, T844I, D912V
Marginally; cross-resistant to cidofovir | HSV-1 pUL30 | V714M, A719V, S724N, L778M, L802F, Y818C, T821M, G841S
Marginally; cross-resistant to cidofovir | HSV-2 pUL30 | L783M

CLINICAL PHARMACOLOGY

Pharmacokinetics

The pharmacokinetics of foscarnet has been determined after administration as an intermittent intravenous infusion during induction therapy in AIDS patients with CMV retinitis. Observed plasma foscarnet concentrations in four studies (FOS-01, ACTG-015, FP48PK, FP49PK) are summarized in Table 7:

TABLE 7 Foscarnet Pharmacokinetic Characteristics*
Parameter | 60 mg/kg Q8h | 90 mg/kg Q12h
Cmax at steady-state (μM) | 589 ± 192 (24) | 623 ± 132 (19)
Ctrough at steady-state (μM) | 114 ± 91 (24) | 63 ± 57 (17)
Volume of distribution (L/kg) | 0.41 ± 0.13 (12) | 0.52 ± 0.20 (18)
Plasma half-life (hr) | 4.0 ± 2.0 (24) | 3.3 ± 1.4 (18)
Systemic clearance (L/hr) | 6.2 ± 2.1 (24) | 7.1 ± 2.7 (18)
Renal clearance (L/hr) | 5.6 ± 1.9 (5) | 6.4 ± 2.5 (13)
CSF: plasma ratio | 0.69 ± 0.19 (9) † | 0.66 ± 0.11 (5) ‡
*Values expressed as mean S.D. (number of subjects studied) for each parameter
†50 mg/kg Q8h for 28 days, samples taken 3 hrs after end of 1 hr infusion (Astra Report 815-04 AC025-1)
‡90 mg/kg Q12hr for 28 days, samples taken 1 hr after end of 2 hr infusion (Hengge et al., 1993)

Distribution

In vitro studies have shown that 14 – 17% of foscarnet is protein bound at plasma drug concentrations of 1 – 1000 μM.

The foscarnet terminal half-life determined by urinary excretion was 87.5 ± 41.8 hours, possibly due to release of foscarnet from bone. Postmortem data on several patients in European clinical trials provide evidence that foscarnet does accumulate in bone in humans; however, the extent to which this occurs has not been determined.

Special Populations

Adults with Impaired Renal Function: The pharmacokinetic properties of foscarnet have been determined in a small group of adult subjects with normal and impaired renal function, as summarized in Table 8:

TABLE 8 Pharmacokinetic Parameters (mean ± S.D.) After a Single 60 mg/kg Dose of FOSCAVIR in 4 Groups* of Adults with Varying Degrees of Renal Function
Parameter | Group 1 (N=6) | Group 2 (N=6) | Group 3 (N=6) | Group 4 (N=4)
Creatinine clearance (mL/min) | 108 ± 16 | 68 ± 8 | 34 ± 9 | 20 ± 4
Foscarnet CL (mL/min/kg) | 2.13 ± 0.71 | 1.33 ± 0.43 | 0.46 ± 0.14 | 0.43 ± 0.26
Foscarnet half-life (hr) | 1.93 ± 0.12 | 3.35 ± 0.87 | 13.0 ± 4.05 | 25.3 ± 18.7
*Group 1 patients had normal renal function defined as a creatinine clearance (CrCl) of >80 mL/min, Group 2 CrCl was 50 – 80 mL/min, Group 3 CrCl was 25 – 49 mL/min and Group 4 CrCl was 10 – 24 mL/min.

Total systemic clearance (CL) of foscarnet decreased and half-life increased with diminishing renal function (as expressed by creatinine clearance). Based on these observations, it is necessary to modify the dosage of foscarnet in patients with renal impairment (see DOSAGE AND ADMINISTRATION).

Drug Interaction

The pharmacokinetics of foscarnet and ganciclovir were not altered in 13 patients receiving either concomitant therapy or daily alternating therapy for maintenance of CMV disease.

There is no clinically significant interaction with zidovudine (AZT), or probenecid.

CLINICAL TRIALS

CMV Retinitis

A prospective, randomized, controlled clinical trial (FOS-03) was conducted in 24 patients with AIDS and CMV retinitis comparing treatment with FOSCAVIR to no treatment. Patients received induction treatment of FOSCAVIR, 60 mg/kg every 8 hours for 3 weeks, followed by maintenance treatment with 90 mg/kg/day until retinitis progression (appearance of a new lesion or advancement of the border of a posterior lesion greater than 750 microns in diameter). All diagnoses and determinations of retinitis progression were made from masked reading of retinal photographs. The 13 patients randomized to treatment with FOSCAVIR had a significant delay in progression of CMV retinitis compared to untreated controls. Median times to retinitis progression from study entry were 93 days (range 21 – >364) and 22 days (range 7 – 42), respectively.

In another prospective clinical trial of CMV retinitis in patients with AIDS (ACTG-915), 33 patients were treated with two to three weeks of FOSCAVIR induction (60 mg/kg TID) and then randomized to either 90 mg/kg/day or 120 mg/kg/day maintenance therapy. The median times from study entry to retinitis progression were not significantly different between the treatment groups, 96 (range 14 – >176) days and 140 (range 16 – >233) days, respectively.

In study ACTG 129/FGCRT SOCA study 107 patients with newly diagnosed CMV retinitis were randomized to treatment with FOSCAVIR (induction: 60 mg/kg TID for 2 weeks; maintenance: 90 mg/kg QD) and 127 were randomized to treatment with ganciclovir (induction: 5 mg/kg BID; maintenance: 5 mg/kg QD). The median time to progression on the two drugs was similar (Fos=59 and Gcv=56 days).

Relapsed CMV Retinitis

The CMV Retinitis Retreatment Trial (ACTG 228/SOCA CRRT) was a randomized, open-label comparison of FOSCAVIR or ganciclovir monotherapy to the combination of both drugs for the treatment of persistently active or relapsed CMV retinitis in patients with AIDS. Subjects were randomized to one of the three treatments: FOSCAVIR 90 mg/kg BID induction followed by 120 mg/kg QD maintenance (Fos); ganciclovir 5 mg/kg BID induction followed by 10 mg/kg QD maintenance (Gcv); or the combination of the two drugs, consisting of continuation of the subject's current therapy and induction dosing of the other drug (as above), followed by maintenance with FOSCAVIR 90 mg/kg QD plus ganciclovir 5 mg/kg QD (Cmb). Assessment of retinitis progression was performed by masked evaluation of retinal photographs. The median times to retinitis progression or death were 39 days for the FOSCAVIR group, 61 days for the ganciclovir group and 105 days for the combination group. For the alternative endpoint of retinitis progression (censoring on death), the median times were 39 days for the FOSCAVIR group, 61 days for the ganciclovir group and 132 days for the combination group. Due to censoring on death, the latter analysis may overestimate the treatment effect. Treatment modifications due to toxicity were more common in the combination group than in the FOSCAVIR or ganciclovir monotherapy groups (see ADVERSE REACTIONS section).

Mucocutaneous Acyclovir Resistant HSV Infections

In a controlled trial, patients with AIDS and mucocutaneous, acyclovir-resistant HSV infection were randomized to either FOSCAVIR (N=8) at a dose of 40 mg/kg TID or vidarabine (N=6) at a dose of 15 mg/kg per day. Eleven patients were nonrandomly assigned to receive treatment with FOSCAVIR because of prior intolerance to vidarabine. Lesions in the eight patients randomized to FOSCAVIR healed after 11 to 25 days; seven of the 11 patients nonrandomly treated with FOSCAVIR healed their lesions in 10 to 30 days. Vidarabine was discontinued because of intolerance (N=4) or poor therapeutic response (N=2). In a second trial, forty AIDS patients and three bone marrow transplant recipients with mucocutaneous, acyclovir-resistant HSV infections were randomized to receive FOSCAVIR at a dose of either 40 mg/kg BID or 40 mg/kg TID. Fifteen of the 43 patients had healing of their lesions in 11 to 72 days with no difference in response between the two treatment groups.

INDICATIONS

CMV Retinitis

FOSCAVIR is indicated for the treatment of CMV retinitis in patients with acquired immunodeficiency syndrome (AIDS). Combination therapy with FOSCAVIR and ganciclovir is indicated for patients who have relapsed after monotherapy with either drug. SAFETY AND EFFICACY OF FOSCAVIR HAVE NOT BEEN ESTABLISHED FOR TREATMENT OF OTHER CMV INFECTIONS (e.g., PNEUMONITIS, GASTROENTERITIS); CONGENITAL OR NEONATAL CMV DISEASE; OR NONIMMUNOCOMPROMISED INDIVIDUALS.

Mucocutaneous Acyclovir Resistant HSV Infections

FOSCAVIR is indicated for the treatment of acyclovir-resistant mucocutaneous HSV infections in immunocompromised patients. SAFETY AND EFFICACY OF FOSCAVIR HAVE NOT BEEN ESTABLISHED FOR TREATMENT OF OTHER HSV INFECTIONS (e.g., RETINITIS, ENCEPHALITIS); CONGENITAL OR NEONATAL HSV DISEASE; OR HSV IN NONIMMUNOCOMPROMISED INDIVIDUALS.

CONTRAINDICATIONS

FOSCAVIR is contraindicated in patients with clinically significant hypersensitivity to foscarnet sodium.

WARNINGS

Renal Impairment

THE MAJOR TOXICITY OF FOSCAVIR IS RENAL IMPAIRMENT (see ADVERSE REACTIONS section). Renal impairment is most likely to become clinically evident during the second week of induction therapy, but may occur at any time during FOSCAVIR treatment. Renal function should be monitored carefully during both induction and maintenance therapy (see PATIENT MONITORING section). Elevations in serum creatinine are usually, but not always, reversible following discontinuation or dose adjustment of FOSCAVIR. Safety and efficacy data for patients with baseline serum creatinine levels greater than 2.8 mg/dL or measured 24-hour creatinine clearances <50 mL/min are limited.

SINCE FOSCAVIR HAS THE POTENTIAL TO CAUSE RENAL IMPAIRMENT, DOSE ADJUSTMENT BASED ON SERUM CREATININE IS NECESSARY. Hydration may reduce the risk of nephrotoxicity. It is recommended that 750–1000 mL of normal saline or 5% dextrose solution should be given prior to the first infusion of FOSCAVIR to establish diuresis. With subsequent infusions, 750–1000 mL of hydration fluid should be given with 90-120 mg/kg of FOSCAVIR, and 500 mL with 40–60 mg/kg of FOSCAVIR. Hydration fluid may need to be decreased if clinically warranted.

After the first dose, the hydration fluid should be administered concurrently with each infusion of FOSCAVIR.

Mineral and Electrolyte Abnormalities

FOSCAVIR has been associated with changes in serum electrolytes including hypocalcemia, hypophosphatemia, hyperphosphatemia, hypomagnesemia, and hypokalemia (see ADVERSE REACTIONS section). FOSCAVIR may also be associated with a dose-related decrease in ionized serum calcium which may not be reflected in total serum calcium. This effect is likely to be related to chelation of divalent metal ions such as calcium by foscarnet. Patients should be advised to report symptoms of low ionized calcium such as perioral tingling, numbness in the extremities and paresthesias. Particular caution and careful management of serum electrolytes is advised in patients with altered calcium or other electrolyte levels before treatment and especially in those with neurologic or cardiac abnormalities and those receiving other drugs known to influence minerals and electrolytes (see PATIENT MONITORING and Drug Interactions sections). Physicians should be prepared to treat these abnormalities and their sequelae such as tetany, seizures or cardiac disturbances. The rate of FOSCAVIR infusion may also affect the decrease in ionized calcium. Therefore, an infusion pump must be used for administration to prevent rapid intravenous infusion (see DOSAGE AND ADMINISTRATION section). Slowing the infusion rate may decrease or prevent symptoms.

Seizures

Seizures related to mineral and electrolyte abnormalities have been associated with FOSCAVIR treatment (see WARNING section; Mineral and Electrolyte Abnormalities). Several cases of seizures were associated with death. Cases of status epilepticus have been reported. Risk factors associated with seizures included impaired baseline renal function, low total serum calcium, and underlying CNS conditions.

Hypersensitivity

Serious acute hypersensitivity reactions (e.g., anaphylactic shock, urticaria, angioedema) have been reported postmarketing in patients receiving FOSCAVIR (see ADVERSE REACTIONS section). If such an acute reaction occurs, therapy should be discontinued and appropriate medical therapy immediately instituted.

QT prolongation and torsade de pointes

FOSCAVIR has been associated with prolongation of the QT interval, an ECG abnormality that has been associated with torsades de pointes, which has been reported during postmarketing surveillance for FOSCAVIR (see ADVERSE REACTIONS section). Some of these patients had confounding risk factors such as underlying cardiac disease, electrolyte abnormalities and other concomitant medications.

Use with caution in patients who have a history of QT prolongation, in patients who are taking medications known to prolong the QT interval (see PRECAUTIONS section), in patients with electrolyte disturbances, or in patients who have other risk factors for QT prolongation. Electrocardiograms (ECGs) and measurement of electrolytes should be obtained prior to treatment initiation and periodically during treatment with FOSCAVIR.

PRECAUTIONS

General

Care must be taken to infuse solutions containing FOSCAVIR only into veins with adequate blood flow to permit rapid dilution and distribution to avoid local irritation (see DOSAGE AND ADMINISTRATION). Local irritation and ulcerations of penile epithelium have been reported in male patients receiving FOSCAVIR, possibly related to the presence of drug in the urine. Cases of male and female genital irritation/ulceration have been reported in patients receiving FOSCAVIR. Adequate hydration with close attention to personal hygiene may minimize the occurrence of such events.

Due to the sodium content of FOSCAVIR (240 micromoles (5.5 mg) of sodium per mL), avoid FOSCAVIR use when intravenous infusion of a large amount of sodium or water may not be tolerated (e.g. in patients with cardiomyopathy). FOSCAVIR should also be avoided in patients on a controlled sodium diet.

Hematopoietic System

Anemia has been reported in 33% of patients receiving FOSCAVIR in controlled studies. Granulocytopenia has been reported in 17% of patients receiving FOSCAVIR in controlled studies; however, only 1% (2/189) were terminated from these studies because of neutropenia.

Information for Patients

CMV Retinitis: Patients should be advised that FOSCAVIR is not a cure for CMV retinitis, and that they may continue to experience progression of retinitis during or following treatment. They should be advised to have regular ophthalmologic examinations.

Mucocutaneous Acyclovir-Resistant HSV Infections: Patients should be advised that FOSCAVIR is not a cure for HSV infections. While complete healing is possible, relapse occurs in most patients. Because relapse may be due to acyclovir-sensitive HSV, sensitivity testing of the viral isolate is advised. In addition, repeated treatment with FOSCAVIR has led to the development of resistance associated with poorer response. In the case of poor therapeutic response, sensitivity testing of the viral isolate also is advised.

Effects on Ability to Drive and Use Machines: Adverse effects such as dizziness and convulsions may occur during FOSCAVIR therapy. Patients who experience seizures, dizziness, somnolence or other adverse reactions that could result in impairment, should be advised to avoid driving or operating machinery.

General: Patients should be informed that the major toxicities of foscarnet are renal impairment, electrolyte disturbances, and seizures, and that dose modifications and possibly discontinuation may be required. The importance of close monitoring while on therapy must be emphasized. Patients should be advised of the importance of reporting to their physicians symptoms of perioral tingling, numbness in the extremities or paresthesias during or after infusion as possible symptoms of electrolyte abnormalities. Patients should also be advised to promptly report any cardiac symptoms. Should such symptoms occur, the infusion of FOSCAVIR should be stopped, appropriate laboratory samples for assessment of electrolyte concentrations obtained, and a physician consulted before resuming treatment. The rate of infusion must be no more than 1 mg/kg/minute. The potential for renal impairment may be minimized by accompanying FOSCAVIR administration with hydration adequate to establish and maintain a diuresis during dosing.

Drug Interactions

A possible drug interaction of FOSCAVIR and intravenous pentamidine has been described. Concomitant treatment of four patients in the United Kingdom with FOSCAVIR and intravenous pentamidine may have caused hypocalcemia; one patient died with severe hypocalcemia. Toxicity associated with concomitant use of aerosolized pentamidine has not been reported. Because FOSCAVIR can reduce serum levels of ionized calcium, extreme caution is advised when used concurrently with other drugs known to influence serum calcium levels (e.g., intravenous pentamidine). Renal impairment and symptomatic hypocalcemia have been observed during concurrent treatment with FOSCAVIR and intravenous pentamidine.

Because of foscarnet's tendency to cause renal impairment, the use of FOSCAVIR should be avoided in combination with potentially nephrotoxic drugs such as aminoglycosides, amphotericin B, cyclosporine, acyclovir, methotrexate, tacrolimus and intravenous pentamidine (see above) unless the potential benefits outweigh the risks to the patient.

When diuretics are indicated, thiazides are recommended over loop diuretics because the latter inhibit renal tubular secretion, and may impair elimination of FOSCAVIR, potentially leading to toxicity.

Abnormal renal function has been observed in clinical practice during the use of FOSCAVIR and ritonavir, or FOSCAVIR, ritonavir, and saquinavir. (See DOSAGE and ADMINISTRATION.)

Because of the risk of QT prolongation and the potential for torsades de pointes, the use of FOSCAVIR should be avoided in combination with agents known to prolong the QT interval including Class IA (e.g., quinidine or procainamide) or Class III (e.g., dofetilide, amiodarone, sotalol) antiarrhythmic agents, phenothiazines, tricyclic antidepressants, and certain macrolides and fluoroquinolones.

Carcinogenesis, Mutagenesis, Impairment of Fertility

Carcinogenicity studies were conducted in rats and mice at oral doses of 500 mg/kg/day and 250 mg/kg/day. Oral bioavailability in unfasted rodents is < 20%. No evidence of oncogenicity was reported at plasma drug levels equal to 1/3 and 1/5, respectively, of those in humans (at the maximum recommended human daily dose) as measured by the area-under-the-time/concentration curve (AUC).

FOSCAVIR showed genotoxic effects in the BALB/3T3 in vitro transformation assay at concentrations greater than 0.5 mcg/mL and an increased frequency of chromosome aberrations in the sister chromatid exchange assay at 1000 mcg/mL. A high dose of foscarnet (350 mg/kg) caused an increase in micronucleated polychromatic erythrocytes in vivo in mice at doses that produced exposures (area under curve) comparable to that anticipated clinically.

Pregnancy

There are no adequate and well-controlled studies of FOSCAVIR in pregnant women. Because animal reproduction studies are not always predictive of human response, this drug should be used during pregnancy only if clearly needed.

Animal Data: FOSCAVIR did not adversely affect fertility and general reproductive performance in rats. The results of peri- and post-natal studies in rats were also negative. However, these studies used exposures that are inadequate to define the potential for impairment of fertility at human drug exposure levels.

Daily subcutaneous doses up to 75 mg/kg administered to female rats prior to and during mating, during gestation, and 21 days post-partum caused a slight increase (< 5%) in the number of skeletal anomalies compared with the control group. Daily subcutaneous doses up to 75 mg/kg administered to rabbits and 150 mg/kg administered to rats during gestation caused an increase in the frequency of skeletal anomalies/variations. On the basis of estimated drug exposure (as measured by AUC), the 150 mg/kg dose in rats and 75 mg/kg dose in rabbits were approximately one-eighth (rat) and one-third (rabbit) the estimated maximal daily human exposure. These studies are inadequate to define the potential teratogenicity at levels to which women will be exposed.

Nursing Mothers

It is not known whether FOSCAVIR is excreted in human milk; however, in lactating rats administered 75 mg/kg, FOSCAVIR was excreted in maternal milk at concentrations three times higher than peak maternal blood concentrations. Because of the potential for serious adverse events in nursing infants, a decision should be made whether to discontinue nursing or discontinue drug, taking into consideration the importance of the drug to the mother. The Centers for Disease Control and Prevention recommend that HIV-infected mothers not breast-feed their infants to avoid risking postnatal transmission of HIV.

Pediatric Use

The safety and effectiveness of FOSCAVIR in pediatric patients have not been established. FOSCAVIR is deposited in teeth and bone and deposition is greater in young and growing animals. FOSCAVIR has been demonstrated to adversely affect development of tooth enamel in mice and rats. The effects of this deposition on skeletal development have not been studied.

Since deposition in human bone has also been shown to occur, it is likely that it does so to a greater degree in developing bone in pediatric patients. Administration to pediatric patients should be undertaken only after careful evaluation and only if the potential benefits for treatment outweigh the risks.

Geriatric Use

No studies of the efficacy or safety of FOSCAVIR in persons 65 years of age or older have been conducted. However, FOSCAVIR has been used in patients age 65 years of age and older. The pattern of adverse events seen in these patients is consistent across all age groups. This drug is known to be substantially excreted by the kidney, and the risk of toxic reactions to this drug may be greater in patients with impaired renal function. Because elderly patients are more likely to have decreased renal function, care should be taken in dose selection, and renal function should be monitored. (See DOSAGE AND ADMINISTRATION).

ADVERSE REACTIONS

THE MAJOR TOXICITY OF FOSCAVIR IS RENAL IMPAIRMENT (see WARNINGS section). Approximately 33% of 189 patients with AIDS and CMV retinitis who received FOSCAVIR (60 mg/kg TID), without adequate hydration, developed significant impairment of renal function (serum creatinine ≥ 2.0 mg/dL). The incidence of renal impairment in subsequent clinical trials in which 1000 mL of normal saline or 5% dextrose solution was given with each infusion of FOSCAVIR was 12% (34/280).

FOSCAVIR has been associated with changes in serum electrolytes including hypocalcemia (15–30%), hypophosphatemia (8–26%) and hyperphosphatemia (6%), hypomagnesemia (15–30%), and hypokalemia (16–48%) (see WARNINGS section). The higher percentages were derived from those patients receiving hydration.

FOSCAVIR treatment was associated with seizures in 18/189 (10%) AIDS patients in the initial five controlled studies (see WARNINGS section). Risk factors associated with seizures included impaired baseline renal function, low total serum calcium, and underlying CNS conditions predisposing the patient to seizures. The rate of seizures did not increase with duration of treatment. Three cases were associated with overdoses of FOSCAVIR (see OVERDOSAGE section).

In five controlled U.S. clinical trials the most frequently reported adverse events in patients with AIDS and CMV retinitis are shown in Table 9. These figures were calculated without reference to drug relationship or severity.

TABLE 9 Adverse Events Reported in Five Controlled US Clinical Trials
 | n = 189 |  | n = 189
Fever | 65% | Abnormal Renal Function | 27%
Nausea | 47% | Vomiting | 26%
Anemia | 33% | Headache | 26%
Diarrhea | 30% | Seizures | 10%

From the same controlled studies, adverse events categorized by investigator as “severe” are shown in Table 10. Although death was specifically attributed to FOSCAVIR in only one case, other complications of FOSCAVIR (i.e., renal impairment, electrolyte abnormalities, and seizures) may have contributed to patient deaths (see WARNINGS section).

TABLE 10 Severe Adverse Events
 | n = 189
Death | 14%
Abnormal Renal Function | 14%
Marrow Suppression | 10%
Anemia | 9%
Seizures | 7%

From the five initial U.S. controlled trials of FOSCAVIR, the following list of adverse events has been compiled regardless of causal relationship to FOSCAVIR. Evaluation of these reports was difficult because of the diverse manifestations of the underlying disease and because most patients received numerous concomitant medications.

Incidence of 5% or Greater

Body as a Whole: fever, fatigue, rigors, asthenia, malaise, pain, infection, sepsis, death

Central and Peripheral Nervous System: headache, paresthesia, dizziness, involuntary muscle contractions, hypoesthesia, neuropathy, seizures including grand mal seizures (see WARNINGS)

Gastrointestinal System: anorexia, nausea, diarrhea, vomiting, abdominal pain

Hematologic: anemia, granulocytopenia, leukopenia, neutropenia (see PRECAUTIONS)

Metabolic and Nutritional: mineral and electrolyte imbalances (see WARNINGS) including hypokalemia, hypocalcemia, hypomagnesemia, hypophosphatemia, hyperphosphatemia

Psychiatric: depression, confusion, anxiety

Respiratory System: coughing, dyspnea

Skin and Appendages: rash, increased sweating

Urinary System: alterations in renal function including increased serum creatinine, decreased creatinine clearance, and abnormal renal function (see WARNINGS)

Special Senses: vision abnormalities

Incidence between 1% and 5%

Application Site: injection site pain, injection site inflammation

Body as a Whole: back pain, chest pain (including reports of transient chest pain as part of infusion reactions), edema, influenza-like symptoms, bacterial infections, moniliasis, fungal infections, abscess

Cardiovascular: hypertension, palpitations, ECG abnormalities including sinus tachycardia, first degree AV block and non-specific ST-T segment changes, hypotension, flushing, cerebrovascular disorder (see WARNINGS)

Central and Peripheral Nervous System: tremor, ataxia, dementia, stupor, generalized spasms, sensory disturbances, meningitis, aphasia, abnormal coordination, leg cramps, EEG abnormalities (see WARNINGS)

Gastrointestinal: constipation, dysphagia, dyspepsia, rectal hemorrhage, dry mouth, melena, flatulence, ulcerative stomatitis, pancreatitis

Hematologic: thrombocytopenia, platelet abnormalities, thrombosis, white blood cell abnormalities, lymphadenopathy

Liver and Biliary: abnormal A-G ratio, abnormal hepatic function, increased SGPT, increased SGOT

Metabolic and Nutritional: hyponatremia, decreased weight, increased alkaline phosphatase, increased LDH, increased BUN, acidosis, cachexia, thirst

Musculo-Skeletal: arthralgia, myalgia

Neoplasms: lymphoma-like disorder, sarcoma

Psychiatric: insomnia, somnolence, nervousness, amnesia, agitation, aggressive reaction, hallucination

Respiratory System: pneumonia, sinusitis, pharyngitis, rhinitis, respiratory disorders, respiratory insufficiency, pulmonary infiltration, stridor, pneumothorax, hemoptysis, bronchospasm

Skin and Appendages: pruritus, skin ulceration, seborrhea, erythematous rash, maculo-papular rash, skin discoloration

Special Senses: taste perversions, eye abnormalities, eye pain, conjunctivitis

Urinary System: albuminuria, dysuria, polyuria, urethral disorder, urinary retention, urinary tract infections, acute renal failure, nocturia, facial edema

Selected adverse events occurring at a rate of less than 1% in the five initial U.S. controlled clinical trials of FOSCAVIR include: syndrome of inappropriate antidiuretic hormone secretion, pancytopenia, hematuria, dehydration, hypoproteinemia, increases in amylase and creatinine phosphokinase, cardiac arrest, coma, and other cardiovascular and neurologic complications.

Selected adverse event data from the Foscarnet vs. Ganciclovir CMV Retinitis Trial (FGCRT), performed by the Studies of the Ocular Complications of AIDS (SOCA) Research Group, are shown in Table 11 (see CLINICAL TRIALS section).

TABLE 11 FGCRT: Selected Adverse Events*
EVENT | GANCICLOVIR |  |  | FOSCARNET
EVENT | No. of Events | No. of Patients | Rates† | No. of Events | No. of Patients | Rates†
Absolute neutrophil count decreasing to <0.50 x 10^9 per liter | 63 | 41 | 1.30 | 31 | 17 | 0.72
Serum creatinine increasing to >260 μmol per liter (>2.9 mg/dL) | 6 | 4 | 0.12 | 13 | 9 | 0.30
Seizure ‡ | 21 | 13 | 0.37 | 19 | 13 | 0.37
Catheterization-related infection | 49 | 27 | 1.26 | 51 | 28 | 1.46
Hospitalization | 209 | 91 | 4.74 | 202 | 75 | 5.03
* Values for the treatment groups refer only to patients who completed at least one follow-up visit – i.e., 133 to 119 patients in the ganciclovir group and 93 to 100 in the foscarnet group. “Events” denotes all events observed and “patients” the number of patients with one or more of the indicated events.
†Per person-year at risk
‡Final frozen SOCA I database dated October 1991

Selected adverse events from ACTG Study 228 (CRRT) comparing combination therapy with FOSCAVIR or ganciclovir monotherapy are shown in Table 12. The most common reason for a treatment change in patients assigned to either FOSCAVIR or ganciclovir was retinitis progression. The most frequent reason for a treatment change in the combination treatment group was toxicity.

TABLE 12 CRRT: Selected Adverse Events
 | Foscavir N=88 |  |  | Ganciclovir N=93 |  |  | Combination N=93
 | No. Events | No. Pts.* | Rate† | No. Events | No. Pts.* | Rate† | No. Events | No. Pts.* | Rate†
Anemia (Hgb <70g/L) | 11 | 7 | 0.20 | 9 | 7 | 0.14 | 19 | 15 | 0.33
Neutropenia‡ ANC <0.75 x 10^9 cells/L ANC <0.50 x 10^9 cells/L | 86 50 | 32 25 | 1.53 0.91 | 95 49 | 41 28 | 1.51 0.80 | 107 50 | 51 28 | 1.91 0.85
Thrombocytopenia Platelets <50 x 10^9/L Platelets <20 x 10^9/L | 28 1 | 14 1 | 0.50 0.01 | 19 6 | 8 2 | 0.43 0.05 | 40 7 | 15 6 | 0.56 0.18
Nephrotoxicity Creatinine >260 μmol/L (>2.9 mg/dL) | 9 | 7 | 0.15 | 10 | 7 | 0.17 | 11 | 10 | 0.20
Seizures | 6 | 6 | 0.17 | 7 | 6 | 0.15 | 10 | 5 | 0.18
Hospitalizations | 86 | 53 | 1.86 | 111 | 59 | 2.36 | 118 | 64 | 2.36
* Pts. = patients with event; †Rate = events/person/year; ‡ANC = absolute neutrophil count

Adverse events that have been reported in post-marketing surveillance include: administration site extravasation, localized edema, hypersensitivity reactions (including anaphylactic shock, urticaria and angioedema) (see WARNINGS section), gastrointestinal hemorrhage, increased lipase, glomerulonephritis, nephrotic syndrome, proteinuria, status epilepticus, ventricular arrhythmia, prolongation of QT interval, torsade de pointes (see WARNINGS section), gamma GT increased, diabetes insipidus (usually nephrogenic), renal calculus, Fanconi syndrome acquired, renal tubular acidosis, renal tubular necrosis, crystal-induced nephropathy, hypercalcemia, hypernatremia, esophageal ulceration and muscle disorders including myopathy, myositis, muscle weakness and rare cases of rhabdomyolysis. Cases of vesiculobullous eruptions including erythema multiforme, toxic epidermal necrolysis, and Stevens-Johnson syndrome have been reported. In most cases, patients were taking other medications that have been associated with toxic epidermal necrolysis or Stevens-Johnson syndrome.

OVERDOSAGE

In controlled clinical trials performed in the United States, overdosage with FOSCAVIR was reported in 10 out of 189 patients. All 10 patients experienced adverse events and all except one made a complete recovery. One patient died after receiving a total daily dose of 12.5 g for three days instead of the intended 10.9 g. The patient suffered a grand mal seizure and became comatose. Three days later the patient expired with the cause of death listed as respiratory/cardiac arrest. The other nine patients received doses ranging from 1.14 times to 8 times their recommended doses with an average of 4 times their recommended doses. Overall, three patients had seizures, three patients had renal function impairment, four patients had paresthesias either in limbs or periorally, and five patients had documented electrolyte disturbances primarily involving calcium and phosphate.

Overdose (up to 20 times the recommended dose) has been reported in post-marketing use of FOSCAVIR. Some of these post-marketing reports were relative overdoses in that the dose of FOSCAVIR had not been adjusted in patients with a reduced renal function. The pattern of adverse events associated with a FOSCAVIR overdose is consistent with the known adverse event profile of the drug.

There is no specific antidote for FOSCAVIR overdose. Hemodialysis and hydration may be of benefit in reducing drug plasma levels in patients who receive an overdosage of FOSCAVIR, but the effectiveness of these interventions has not been evaluated. The patient should be observed for signs and symptoms of renal impairment and electrolyte imbalance. Medical treatment should be instituted if clinically warranted.

DOSAGE AND ADMINISTRATION

CAUTION - DO NOT ADMINISTER FOSCAVIR BY RAPID OR BOLUS INTRAVENOUS INJECTION. THE TOXICITY OF FOSCAVIR MAY BE INCREASED AS A RESULT OF EXCESSIVE PLASMA LEVELS. CARE SHOULD BE TAKEN TO AVOID UNINTENTIONAL OVERDOSE BY CAREFULLY CONTROLLING THE RATE OF INFUSION. THEREFORE, AN INFUSION PUMP MUST BE USED. IN SPITE OF THE USE OF AN INFUSION PUMP, OVERDOSES HAVE OCCURRED.

ADMINISTRATION

Instructions for Administration and Preparation

FOSCAVIR is administered by controlled intravenous infusion, either by using a central venous line or by using a peripheral vein. The rate of infusion must be no more than 1 mg/kg/minute. An individualized dose of FOSCAVIR should be calculated on the basis of body weight (mg/kg), renal function, indication of use and dosing frequency (refer to DOSAGE subsection). To reduce the risk of nephrotoxicity, creatinine clearance (mL/min/kg) should be calculated even if serum creatinine is within the normal range, and doses should be adjusted accordingly.

An individualized dose at the required concentration (24 mg/mL or 12 mg/mL) for the route of administration (central line or peripheral line) needs to be aseptically prepared prior to dispensing. The standard 24 mg/mL solution may be used with or without dilution when using a central venous catheter for infusion. When a peripheral vein catheter is used, the 24 mg/mL injection must be diluted to a 12 mg/mL concentration with 5% dextrose in water or with a normal saline solution prior to administration to avoid local irritation of peripheral veins. Dilutions and/or removals of excess quantities should be accomplished under aseptic conditions. Solutions thus prepared should be used within 24 hours of first entry into a sealed bottle or infusion bag.

Hydration

Hydration may reduce the risk of nephrotoxicity. Clinically dehydrated patients should have their condition corrected before initiating FOSCAVIR therapy. It is recommended that 750–1000 mL of normal saline or 5% dextrose solution should be given prior to the first infusion of FOSCAVIR to establish diuresis. With subsequent infusions, 750–1000 mL of hydration fluid should be given with 90–120 mg/kg of FOSCAVIR, and 500 mL with 40–60 mg/kg of FOSCAVIR. Hydration fluid may need to be decreased if clinically warranted. Oral rehydration with similar regimens may be considered in certain patients.

After the first dose, the hydration fluid should be administered concurrently with each infusion of FOSCAVIR.

Compatibility With Other Solutions/Drugs

Other drugs and supplements can be administered to a patient receiving FOSCAVIR. However, care must be taken to ensure that FOSCAVIR is only administered with normal saline or 5% dextrose solution and that no other drug or supplement is administered concurrently via the same catheter. Foscarnet has been reported to be chemically incompatible with 30% dextrose, amphotericin B, and solutions containing calcium such as Ringer's lactate and TPN. Physical incompatibility with other IV drugs has also been reported including acyclovir sodium, ganciclovir, trimetrexate glucuronate, pentamidine isethionate, vancomycin, trimethoprim/sulfamethoxazole, diazepam, midazolam, digoxin, phenytoin, leucovorin, and proclorperazine. Because of foscarnet's chelating properties, a precipitate can potentially occur when divalent cations are administered concurrently in the same catheter.

Parenteral drug products must be inspected visually for particulate matter and discoloration prior to administration whenever the solution and container permit. Solutions that are discolored or contain particulate matter should not be used.

Accidental Exposure

Accidental skin and eye contact with foscarnet sodium solution may cause local irritation and burning sensation. If accidental contact occurs, the exposed area should be flushed with water.

DOSAGE

THE RECOMMENDED DOSAGE, FREQUENCY, OR INFUSION RATES SHOULD NOT BE EXCEEDED. ALL DOSES MUST BE INDIVIDUALIZED FOR PATIENTS' RENAL FUNCTION.

Induction Treatment

The recommended initial dose of FOSCAVIR for patients with normal renal function is:

- For CMV retinitis patients, either 90 mg/kg (1-1/2 to 2 hour infusion) every twelve hours or 60 mg/kg (minimum one hour infusion) every eight hours over 2-3 weeks depending on clinical response.
- For acyclovir-resistant HSV patients, 40 mg/kg (minimum one hour infusion) either every 8 or 12 hours for 2-3 weeks or until healed.

An infusion pump must be used to control the rate of infusion. Adequate hydration is recommended to establish a diuresis (see Hydration for recommendation), both prior to and during treatment to minimize renal toxicity (see WARNINGS), provided there are no clinical contraindications.

Maintenance Treatment

Following induction treatment the recommended maintenance dose of FOSCAVIR for CMV retinitis is 90 mg/kg/day to 120 mg/kg/day (individualized for renal function) given as an intravenous infusion over 2 hours. Because the superiority of the 120 mg/kg/day has not been established in controlled trials, and given the likely relationship of higher plasma foscarnet levels to toxicity, it is recommended that most patients be started on maintenance treatment with a dose of 90 mg/kg/day. Escalation to 120 mg/kg/day may be considered should early reinduction be required because of retinitis progression. Some patients who show excellent tolerance to FOSCAVIR may benefit from initiation of maintenance treatment at 120 mg/kg/day earlier in their treatment.

An infusion pump must be used to control the rate of infusion with all doses. Again, hydration to establish diuresis both prior to and during treatment is recommended to minimize renal toxicity, provided there are no clinical contraindications (see WARNINGS).

Patients who experience progression of retinitis while receiving FOSCAVIR maintenance therapy may be retreated with the induction and maintenance regimens given above or with a combination of FOSCAVIR and ganciclovir (see CLINICAL TRIALS section). Because of physical incompatibility, FOSCAVIR and ganciclovir must NOT be mixed.

Use in Patients with Abnormal Renal Function

FOSCAVIR should be used with caution in patients with abnormal renal function because reduced plasma clearance of foscarnet will result in elevated plasma levels (see CLINICAL PHARMACOLOGY). In addition, FOSCAVIR has the potential to further impair renal function (see WARNINGS). Safety and efficacy data for patients with baseline serum creatinine levels greater than 2.8 mg/dL or measured 24-hour creatinine clearances < 50 mL/min are limited.

Renal function must be monitored carefully at baseline and during induction and maintenance therapy with appropriate dose adjustments for FOSCAVIR as outlined below (see Dose Adjustment and PATIENT MONITORING). During FOSCAVIR therapy if creatinine clearance falls below the limits of the dosing nomograms (0.4 mL/min/kg), FOSCAVIR should be discontinued, the patient hydrated, and monitored daily until resolution of renal impairment is ensured.

FOSCAVIR is not recommended in patients undergoing hemodialysis because dosage guidelines have not been established.

Dose Adjustment

FOSCAVIR dosing must be individualized according to the patient's renal function status. Refer to Table 13 below for recommended doses and adjust the dose as indicated. Even patients with serum creatinine in the normal range may require dose adjustment; therefore, the dose should be calculated at baseline and frequently thereafter.

To use this dosing guide, actual 24-hour creatinine clearance (mL/min) must be divided by body weight (kg), or the estimated creatinine clearance in mL/min/kg can be calculated from serum creatinine (mg/dL) using the following formula (modified Cockcroft and Gault equation):

For males: 140 – age (x 0.85 for females) = mL/min/kg
Serum creatinine x 72

TABLE 13 FOSCAVIR Dosage Guide Induction
 | HSV: Equivalent to |  | CMV: Equivalent to
CrCI (mL/min/kg) | 80 mg/kg/day total (40 mg/kg Q12h) | 120 mg/kg/day total (40 mg/kg Q8h) | 180 mg/kg/day total
CrCI (mL/min/kg) | 80 mg/kg/day total (40 mg/kg Q12h) | 120 mg/kg/day total (40 mg/kg Q8h) | (60 mg/kg Q8h) | (90 mg/kg Q12h)
>1.4 | 40 Q12h | 40 Q8h | 60 Q8h | 90 Q12h
>1.0 – 1.4 | 30 Q12h | 30 Q8h | 45 Q8h | 70 Q12h
>0.8 – 1.0 | 20 Q12h | 35 Q12h | 50 Q12h | 50 Q12h
>0.6 – 0.8 | 35 Q24h | 25 Q12h | 40 Q12h | 80 Q24h
>0.5 – 0.6 | 25 Q24h | 40 Q24h | 60 Q24h | 60 Q24h
>0.4 – 0.5 | 20 Q24h | 35 Q24h | 50 Q24h | 50 Q24h
<0.4 | Not recommended | Not recommended | Not recommended | Not recommended

Maintenance
 | CMV: Equivalent to
CrCI (mL/min/kg) | 90 mg/kg/day (once daily) | 120 mg/kg/day (once daily)
>*1.4 | 90 Q24h | 120 Q24h
>*1.0 – 1.4 | 70 Q24h | 90 Q24h
>*0.8 – 1.0 | 50 Q24h | 65 Q24h
>*0.6 – 0.8 | 80 Q48h | 105 Q48h
>*0.5 – 0.6 | 60 Q48h | 80 Q48h
≥†0.4 – 0.5 | 50 Q48h | 65 Q48h
<‡0.4 | Not recommended | Not recommended
*> means “greater than”, †≥ means “greater than or equal to”, ‡< means “less than”

PATIENT MONITORING

The majority of patients will experience some decrease in renal function due to FOSCAVIR administration. Therefore it is recommended that creatinine clearance, either measured or estimated using the modified Cockcroft and Gault equation based on serum creatinine, be determined at baseline, 2–3 times per week during induction therapy and once weekly during maintenance therapy, with FOSCAVIR dose adjusted accordingly (see Dose Adjustment). More frequent monitoring may be required for some patients. It is also recommended that a 24-hour creatinine clearance be determined at baseline and periodically thereafter to ensure correct dosing (assuming verification of an adequate collection using creatinine index). FOSCAVIR should be discontinued if creatinine clearance drops below 0.4 mL/min/kg.

Due to FOSCAVIR's propensity to chelate divalent metal ions and alter levels of serum electrolytes, patients must be monitored closely for such changes. It is recommended that a schedule similar to that recommended for serum creatinine (see above) be used to monitor serum calcium, magnesium, potassium and phosphorus. Particular caution is advised in patients with decreased total serum calcium or other electrolyte levels before treatment, as well as in patients with neurologic or cardiac abnormalities, and in patients receiving other drugs known to influence serum calcium levels. Any clinically significant metabolic changes should be corrected. Also, patients who experience mild (e.g., perioral numbness or paresthesias) or severe (e.g., seizures) symptoms of electrolyte abnormalities should have serum electrolyte and mineral levels assessed as close in time to the event as possible.

Careful monitoring and appropriate management of electrolytes, calcium, magnesium and creatinine are of particular importance in patients with conditions that may predispose them to seizures (see WARNINGS).

HOW SUPPLIED

FOSCAVIR (foscarnet sodium) INJECTION, 24 mg/mL for intravenous infusion, is supplied in 250 mL glass bottles or polypropylene based infusion bags containing 6000 mg foscarnet sodium (24 mg/mL) as follows:

NDC 76310-024-11 250 mL bottle
NDC 76310-024-01 250 mL bottles, cases of 10
NDC 76310-024-31 250 mL infusion bag
NDC 76310-024-35 250 mL infusion bag, cases of 10

Single-dose. Discard unused portion.

Store between 20° and 25°C (68° and 77°F) [See USP Controlled Room Temperature]. Protect from excessive heat (above 40°C) and from freezing. If refrigerated or exposed to temperatures below the freezing point, precipitation may occur. By keeping the bottle or infusion bag at room temperature with repeated shaking, the precipitate can be brought into solution again.

FOSCAVIR INJECTION should be used only if the bottle or infusion bag and its seal(s) are intact, a vacuum is present, and the solution is clear and colorless. Do not remove the infusion bag from the overwrap until ready for use.

Manufactured for:
Clinigen Healthcare Ltd., DE14 2WW, UK

Distributed by: Hospira, Inc., Lake Forest, IL 60045 USA

FOSCAVIR is a trademark of Clinigen Healthcare Ltd.

Date of revision: October 2020

Novaplus is a registered trademark of Vizient, Inc.

BOTTLE LABEL – PRINCIPAL DISPLAY PANEL

NDC 76310-024-11

Foscavir ® (foscarnet sodium) injection
6000 mg/250 mL (24 mg/mL)

For Central Intravenous Infusion Only
Must Be Diluted for Peripheral Intravenous Infusion

Rx only
Single-dose. Discard unused portion.

Mfd. for: Clinigen Healthcare Ltd., DE14 2WW, UK.
Distributed by: Hospira Inc., Lake Forest, IL 60045 USA.

(Clinigen and Novaplus logos)

Novaplus is a registered trademark of Vizient, Inc.

INNER CARTON LABEL – PRINCIPAL DISPLAY PANEL

NDC 76310-024-11 Rx only

Foscavir ®
(foscarnet sodium)

injection
6000 mg/250 mL

(24 mg/mL)

For Central Intravenous Infusion Only
Must Be Diluted for Peripheral
Intravenous Infusion

Single-dose. Discard unused portion.